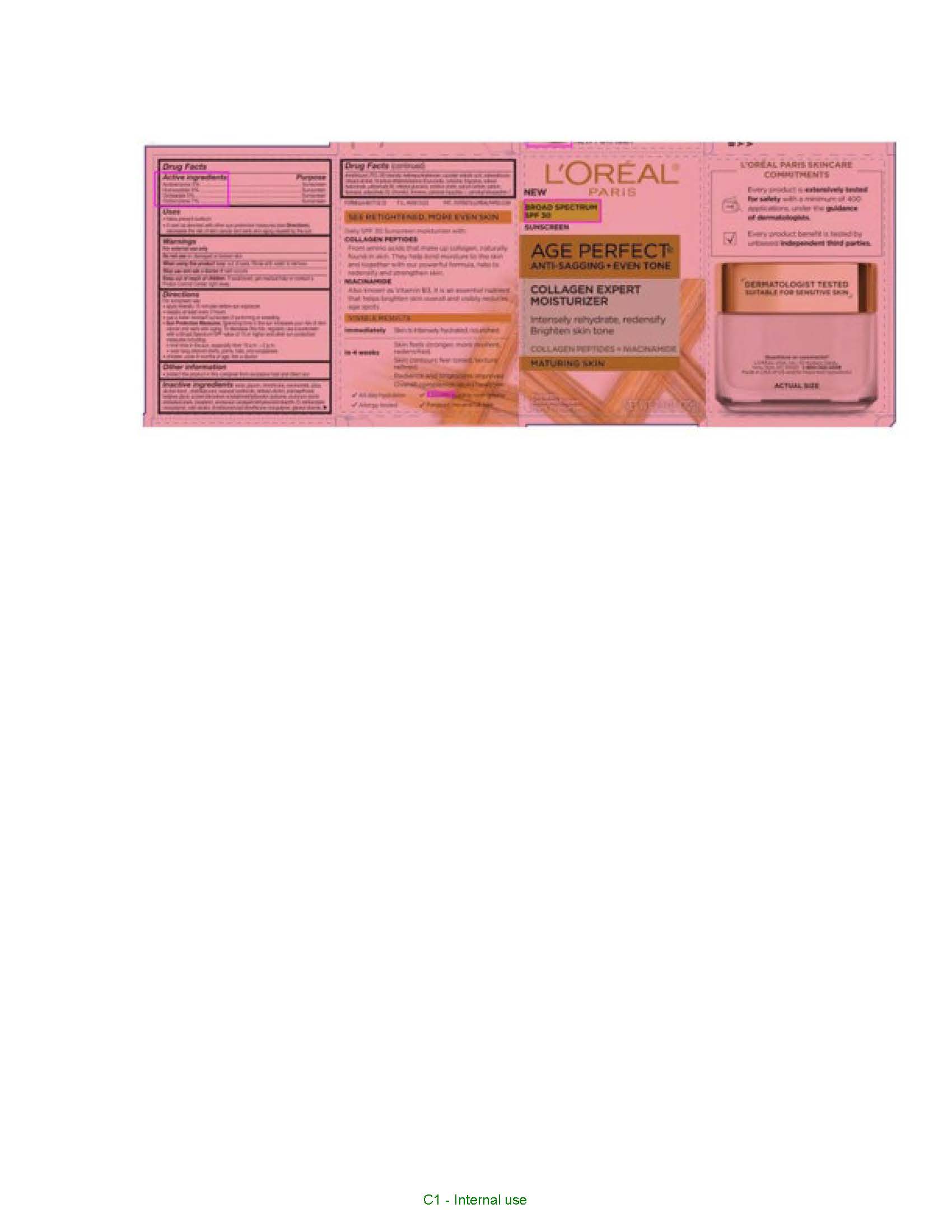 DRUG LABEL: LOreal Paris AntiSagging Plus Even Tone Collagen Expert Moisturizer Broad Spectrum SPF 30 Sunscreen
NDC: 49967-148 | Form: CREAM
Manufacturer: L'Oreal USA Products Inc
Category: otc | Type: HUMAN OTC DRUG LABEL
Date: 20240115

ACTIVE INGREDIENTS: Avobenzone 30 mg/1 g; Homosalate 50 mg/1 g; Octisalate 50 mg/1 g; Octocrylene 70 mg/1 g
INACTIVE INGREDIENTS: WATER; GLYCERIN; DIMETHICONE; NIACINAMIDE; SILICON DIOXIDE; ALCOHOL; OCTYLDODECANOL; ISOPROPYL ISOSTEARATE; DOCOSANOL; CAPRYLOYL SALICYLIC ACID; HYDROXYACETOPHENONE; PALMITOYL TETRAPEPTIDE-7; PALMITOYL TRIPEPTIDE-1; HYALURONATE SODIUM; SODIUM HYDROXIDE; TRISODIUM ETHYLENEDIAMINE DISUCCINATE; TOCOPHEROL; CETYL ALCOHOL; ALUMINUM STARCH OCTENYLSUCCINATE; BUTYLENE GLYCOL; CARBOMER HOMOPOLYMER, UNSPECIFIED TYPE; CETOSTEARYL ALCOHOL; CETEARYL GLUCOSIDE; GLYCERYL MONOSTEARATE; ISOHEXADECANE; PEG-100 STEARATE; POLYSORBATE 20; POLYSORBATE 80; SODIUM LACTATE; SORBITAN MONOOLEATE; DIMETHICONE/VINYL DIMETHICONE CROSSPOLYMER (HARD PARTICLE); DIMETHICONOL (100000 CST); .BETA.-CITRONELLOL, (R)-; LIMONENE, (+)-; PHENOXYETHANOL

Drug Facts

Active ingredients

Avobenzone 3%

Homosalate 5%

Octisalate 5%

Octocrylene 7%

Purpose

Sunscreen

Uses

- helps prevent sunburn
- if used as directed with other sun protection measures (see Directions), decreases the risk of skin cancer and early skin aging caused by the sun

Warnings

For external use only

Do not use

on damaged or broken skin

When using this product

keep out of eyes. Rinse with water to remove.

Stop use and ask a doctor if

rash occurs

Keep out of reach of children.

If swallowed, get medical help or contact a Poison Control Center right away.

Directions

For sunscreen use:
● apply liberally 15 minutes before sun exposure
● reapply at least every 2 hours
● use a water resistant sunscreen if swimming or sweating
● Sun Protection Measures. Spending time in the sun increases your risk of skin cancer and early skin aging. To decrease this risk, regularly use a sunscreen with a Broad Spectrum SPF value of 15 or higher and other sun protection measures including:
● limit time in the sun, especially from 10 a.m. – 2 p.m.
● wear long-sleeved shirts, pants, hats, and sunglasses
● children under 6 months of age: Ask a doctor

Other information

protect the product in this container from excessive heat and direct sun

Inactive ingredients

water, glycerin, dimethicone, niacinamide, silica, alcohol denat., octyldodecanol, isopropyl isostearate, behenyl alcohol, capryloyl salicylic acid, hydroxyacetophenone, palmitoyl tetrapeptide-7, palmitoyl tripeptide-1, sodium hyaluronate, sodium hydroxide, trisodium ethylenediamine disuccinate, tocopherol, cetyl alcohol, acrylamide/sodium acryloyldimethyltaurate copolymer, aluminum starch octenylsuccinate, ammonium acryloyldimethyltaurate/steareth-25 methacrylate crosspolymer, butylene glycol, carbomer, cetearyl alcohol, cetearyl glucoside, glyceryl stearate, isohexadecane, PEG-100 stearate, polysorbate 20, polysorbate 80, sodium lactate, sorbitan oleate, dimethicone/vinyl dimethicone crosspolymer, dimethiconol, citronellol, limonene, phenoxyethanol, fragrance